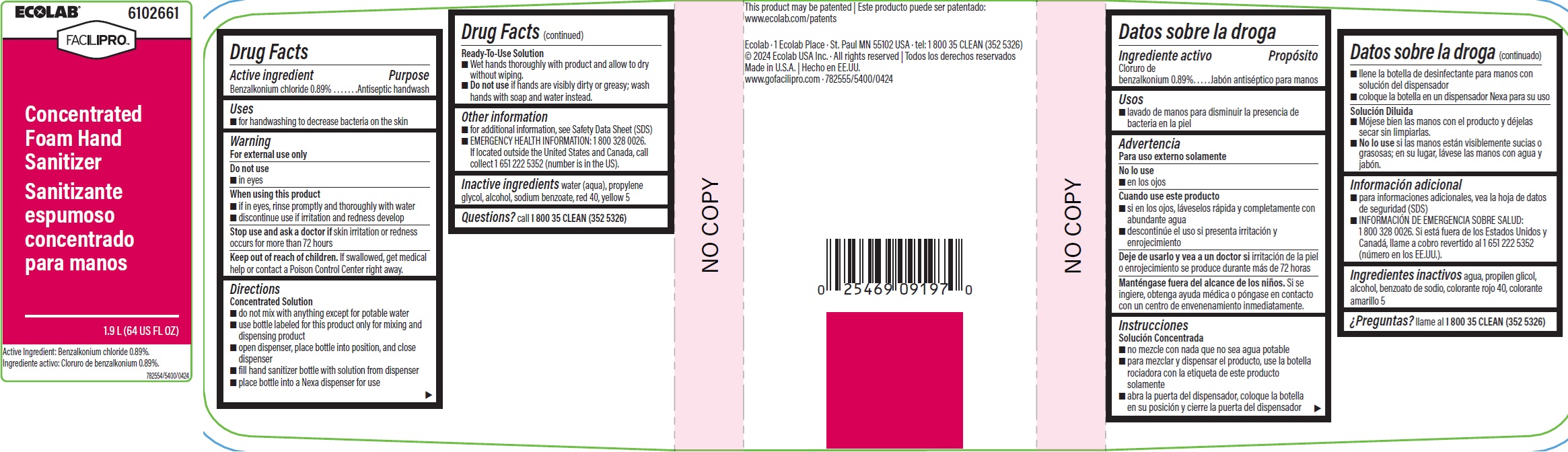 DRUG LABEL: Ecolab Inc.
NDC: 47593-514 | Form: SOLUTION
Manufacturer: Ecolab Inc.
Category: otc | Type: HUMAN OTC DRUG LABEL
Date: 20240712

ACTIVE INGREDIENTS: BENZALKONIUM CHLORIDE 8.9 mg/1 mL
INACTIVE INGREDIENTS: WATER; PROPYLENE GLYCOL; ALCOHOL; SODIUM BENZOATE; FD&C RED NO. 40; FD&C YELLOW NO. 5

Drug Facts

Active ingredient

Benzalkonium chloride 0.89%

Purpose

Antispetic handwash

Uses

- For handwashing to decrease bacteria on the skin

Warning

For external use only

Do not use

- in eyes

Directions: Concentrated Solution

- do not mix with anything except for potable water
- use bottle labeled for this product only for mixing and dispensing product
- open dispenser, place bottle into position, and close dispenser
- fill hand sanitizer bottle with solution from dispenser
- place bottle into a Nexa dispenser for use

Directions

Ready-To-Use Solution

- Wet hands thoroughly with product and allow to dry without wiping.
- Do not use if hands are visibly dirty or greasy; wash hands with soap and water instead.

Other information

- for additional information, see Safety Data Sheet (SDS)
- EMERGENCY HEALTH INFORMATION: 1 800 328 0026. If located outside the United States and Canada, call collect 1 651 222 5352 (number is in the US).

INACTIVE INGREDIENT

Inactive ingredients water (aqua), propylene glycol, alcohol, sodium benzoate, red 40, yellow 5

Questions? call1-800-35-CLEAN (352-5326)

Principal display panel and representative label

ECOLAB 6102661

FACILIPRO

Concentrated

Foam Hand

Sanitizer

1.9 L (64 US FL OZ)

Active Ingredient: Benzalkonium chloride 0.89%

782554/5400/0424

Ecolab · 1 Ecolab Place · St. Paul MN 55102 USA · tel: 1 800 35 CLEAN (352 5326)

© 2024 Ecolab USA Inc. · All rights reserved

Made in U.S.A.

www.gofacilipro.com · 782555/5400/0424